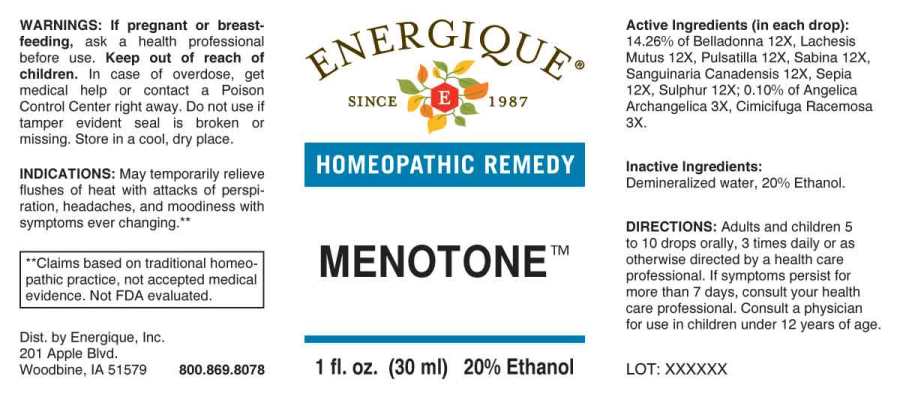 DRUG LABEL: Menotone
NDC: 44911-0258 | Form: LIQUID
Manufacturer: Energique, Inc.
Category: homeopathic | Type: HUMAN OTC DRUG LABEL
Date: 20240123

ACTIVE INGREDIENTS: ANGELICA ARCHANGELICA ROOT 3 [hp_X]/1 mL; BLACK COHOSH 3 [hp_X]/1 mL; ATROPA BELLADONNA 12 [hp_X]/1 mL; LACHESIS MUTA VENOM 12 [hp_X]/1 mL; PULSATILLA PRATENSIS WHOLE 12 [hp_X]/1 mL; JUNIPERUS SABINA LEAFY TWIG 12 [hp_X]/1 mL; SANGUINARIA CANADENSIS ROOT 12 [hp_X]/1 mL; SEPIA OFFICINALIS JUICE 12 [hp_X]/1 mL; SULFUR 12 [hp_X]/1 mL
INACTIVE INGREDIENTS: WATER; ALCOHOL

DRUG FACTS:

ACTIVE INGREDIENTS:

(in each drop): 14.26% of Belladonna 12X, Lachesis Mutus 12X, Pulsatilla (Pratensis) 12X, Sabina 12X, Sanguinaria Canadensis 12X, Sepia 12X, Sulphur 12X; 0.10% of Angelica Archangelica 3X, Cimicifuga Racemosa 3X.

INDICATIONS:

May temporarily relieve flushes of heat with attacks of perspiration, headaches, and moodiness with symptoms ever changing.**

**Claims based on traditional homeopathic practice, not accepted medical evidence. Not FDA evaluated.

WARNINGS:

If pregnant or breast-feeding, ask a health professional before use.

Keep out of reach of children. In case of overdose, get medical help or contact a Poison Control Center right away.

Do not use if tamper evident seal is broken or missing. Store in a cool, dry place.

KEEP OUT OF REACH OF CHILDREN:

In case of overdose, get medical help or contact a Poison Control Center right away.

DIRECTIONS:

Adults and children 5 to 10 drops orally, 3 times daily or as otherwise directed by a health care professional. If symptoms persist for more than 7 days, consult your health care professional. Consult a physician for use in children under 12 years of age.

INDICATIONS:

May temporarily relieve flushes of heat with attacks of perspiration, headaches, and moodiness with symptoms ever changing.**

**Claims based on traditional homeopathic practice, not accepted medical evidence. Not FDA evaluated.

INACTIVE INGREDIENTS:

Demineralized water, 20% Ethanol.

QUESTIONS:

Dist. by Energique, Inc.

201 Apple Blvd

Woodbine, IA 51579 800.869.8078

PACKAGE LABEL DISPLAY:

ENERGIQUE

SINCE 1987

HOMEOPATHIC REMEDY

MENOTONE

1 fl. oz. (30 ml)